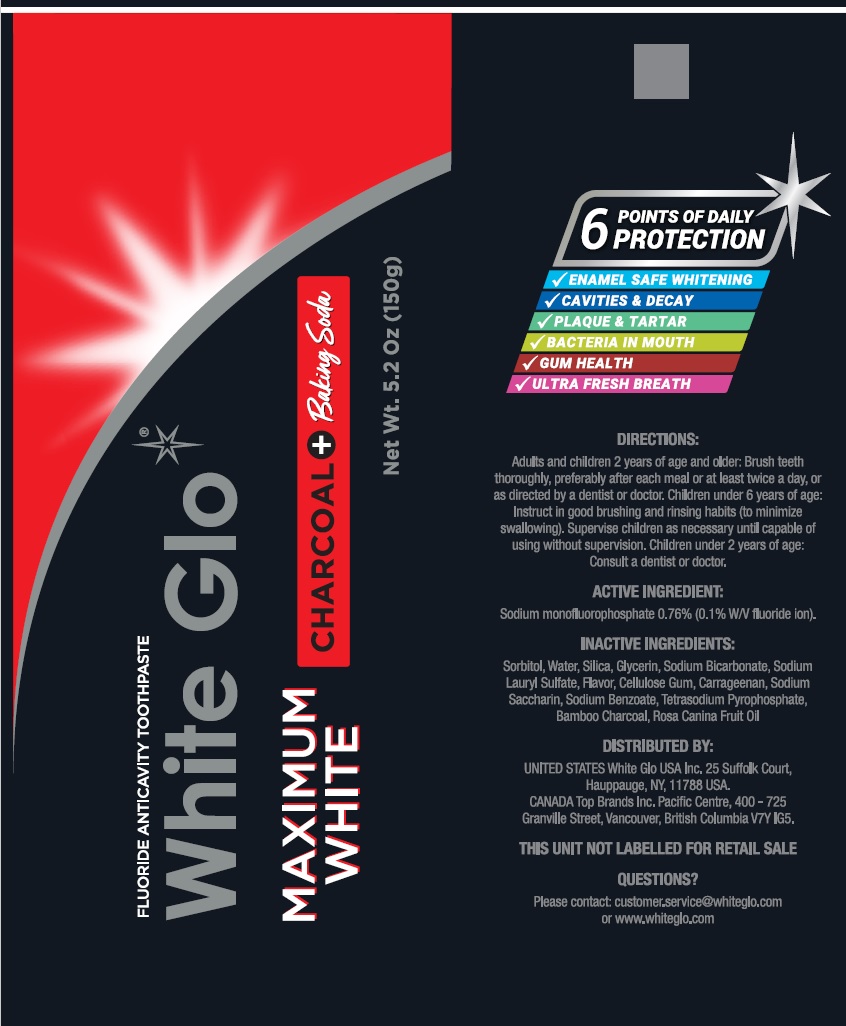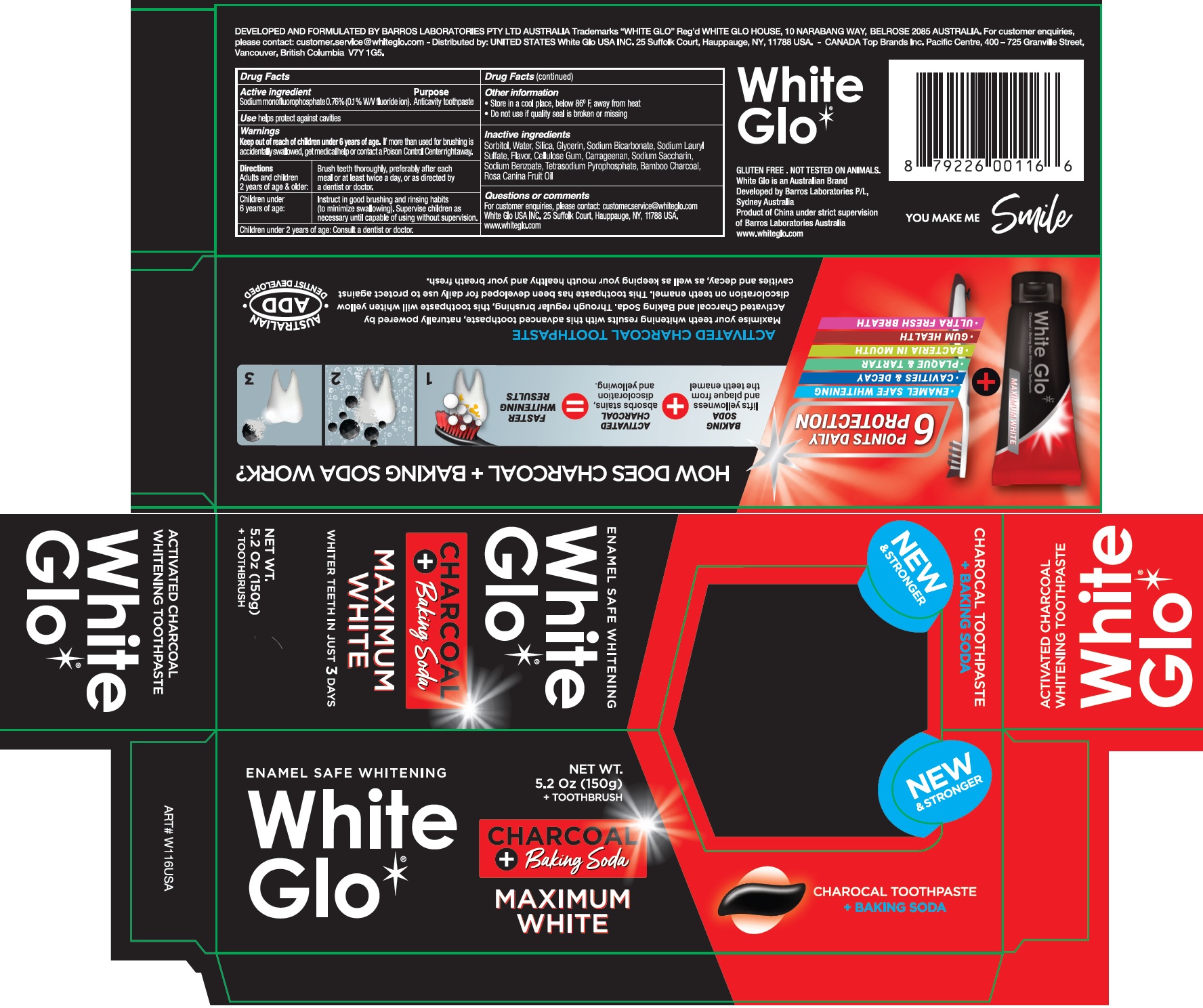 DRUG LABEL: White Glo Maximum White Charcoal
NDC: 73656-013 | Form: KIT | Route: DENTAL
Manufacturer: WHITE GLO USA INC
Category: otc | Type: HUMAN OTC DRUG LABEL
Date: 20250226

ACTIVE INGREDIENTS: SODIUM MONOFLUOROPHOSPHATE 1 mg/1 g
INACTIVE INGREDIENTS: SORBITOL; WATER; SILICON DIOXIDE; GLYCERIN; SODIUM BICARBONATE; SODIUM LAURYL SULFATE; CARBOXYMETHYLCELLULOSE SODIUM, UNSPECIFIED; CARRAGEENAN; SACCHARIN SODIUM; SODIUM BENZOATE; SODIUM PYROPHOSPHATE; ACTIVATED CHARCOAL; ROSA CANINA FRUIT OIL

White Glo Maximum White Toothpaste Charcoal + toothbrush

Active ingredient

Sodium monofluorophosphate 0.76%(0.1% W/V fluoride ion)

Purpose

Anticavity toothpaste

Use

helps pretect against cavities

Warnings

Keep out of reach of children

If more than used for brushing is accidentally swallowed, get medical help or contact a Poison Control Center rightaway. under 6 years of age.

Directions

Adults and children 2 years of age & older: | Brush teeth thoroughly, preferably after each meal or at least twice a day, or as directed by a dentist or doctor.
Children under 6 years of age: | Instruct in good brushing and rinsing habits (to minimize swallowing). Supervise children as necessary until capable of using without supervision.

Children under 2 years of age: Consult a dentist or doctor.

Other information

- Store in a cool place, below 86°F, away from heat
- Do not use if quality seal is broken or missing

Inactive ingredients

Sorbitol, Water, Silica, Glycerin, Sodium Bicarbonate, Sodium Lauryl Sulfate, Flavor, Cellulose Gum, Carrageenan, Sodium Saccharin, Sodium Benzoate, Tetrasodium Pyrophosphate, Bamboo Charcoal, Rosa Canina Fruit Oil

Questions or comments

For customer enquiries, please contact:customer.service@whiteglo.com White Glo USA INC. 25 Suffolk Court, Hauppauge, NY, 11788 USA. www.whiteglo.com